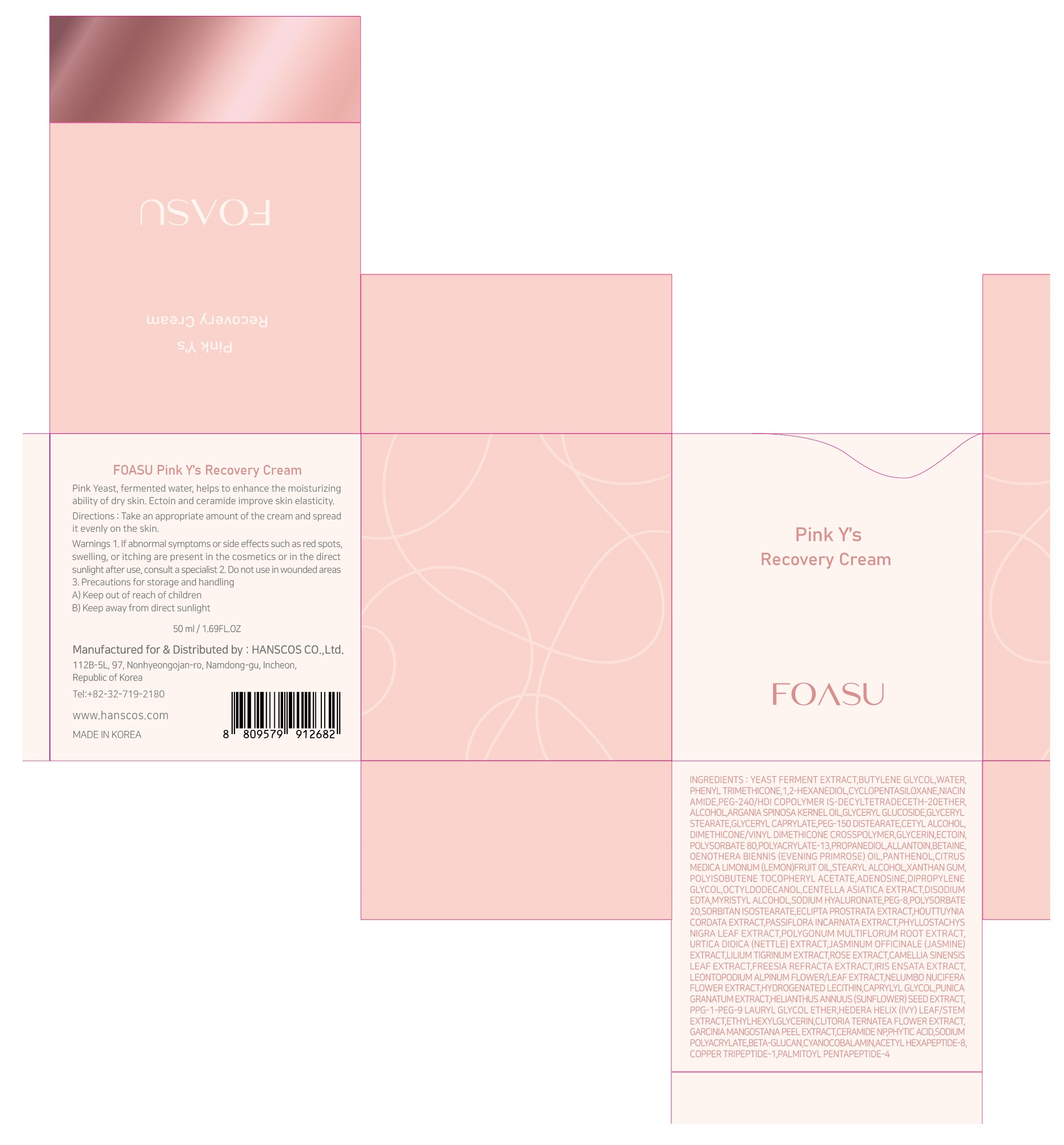 DRUG LABEL: FOASU Pink Y s RecoveryCream
NDC: 77964-004 | Form: CREAM
Manufacturer: HANSCOS Co.,Ltd.
Category: otc | Type: HUMAN OTC DRUG LABEL
Date: 20220227

ACTIVE INGREDIENTS: ADENOSINE 0.04 g/100 mL; NIACINAMIDE 2 g/100 mL
INACTIVE INGREDIENTS: WATER; GLYCERIN

Active ingredient

niacinamide, adenosine

Purpose

skin protectant

Use

apply proper amount to the skin

Warnings

For external use only

1) Please consult your doctor if you experience side effects such as swelling, itching, or reddening on the area where you applied this product

2) Do not apply on wounds or cuts. 3) Do not store where children may reach, and avoid keeping it exposed to direct sunlight.

Directions

for external use only

Inactive ingredients

YEAST FERMENT EXTRACT
BUTYLENE GLYCOL
WATER
PHENYL TRIMETHICONE
1,2-HEXANEDIOL
CYCLOPENTASILOXANE
PEG-240/HDI COPOLYMER BIS-DECYLTETRADECETH-20 ETHER
ALCOHOL
ARGANIA SPINOSA KERNEL OIL
GLYCERYL GLUCOSIDE
GLYCERYL STEARATE
GLYCERYL CAPRYLATE
PEG-150 DISTEARATE
CETYL ALCOHOL
DIMETHICONE/VINYL DIMETHICONE CROSSPOLYMER
GLYCERIN
ECTOIN
POLYSORBATE 80
POLYACRYLATE-13
PROPANEDIOL
ALLANTOIN
BETAINE
OENOTHERA BIENNIS (EVENING PRIMROSE) OIL
PANTHENOL
CITRUS MEDICA LIMONUM (LEMON) FRUIT OIL
STEARYL ALCOHOL
XANTHAN GUM
POLYISOBUTENE
TOCOPHERYL ACETATE
DIPROPYLENE GLYCOL
OCTYLDODECANOL
CENTELLA ASIATICA EXTRACT
DISODIUM EDTA
MYRISTYL ALCOHOL
SODIUM HYALURONATE
PEG-8
POLYSORBATE 20
SORBITAN ISOSTEARATE
ECLIPTA PROSTRATA EXTRACT
HOUTTUYNIA CORDATA EXTRACT
PASSIFLORA INCARNATA EXTRACT
PHYLLOSTACHYS NIGRA LEAF EXTRACT
POLYGONUM MULTIFLORUM ROOT EXTRACT
URTICA DIOICA (NETTLE) EXTRACT
JASMINUM OFFICINALE (JASMINE) EXTRACT
LILIUM TIGRINUM EXTRACT
ROSE EXTRACT
CAMELLIA SINENSIS LEAF EXTRACT
FREESIA REFRACTA EXTRACT
IRIS ENSATA EXTRACT
LEONTOPODIUM ALPINUM FLOWER/LEAF EXTRACT
NELUMBO NUCIFERA FLOWER EXTRACT
HYDROGENATED LECITHIN
CAPRYLYL GLYCOL
PUNICA GRANATUM EXTRACT
HELIANTHUS ANNUUS (SUNFLOWER) SEED EXTRACT
PPG-1-PEG-9 LAURYL GLYCOL ETHER
HEDERA HELIX (IVY) LEAF/STEM EXTRACT
ETHYLHEXYLGLYCERIN
CLITORIA TERNATEA FLOWER EXTRACT
GARCINIA MANGOSTANA PEEL EXTRACT
CERAMIDE NP
PHYTIC ACID
SODIUM POLYACRYLATE
BETA-GLUCAN
CYANOCOBALAMIN
ACETYL HEXAPEPTIDE-8
COPPER TRIPEPTIDE-1
PALMITOYL PENTAPEPTIDE-4

Keep out of reach of children. If swallowed, get medical help or contact a Poison Control Center right away.